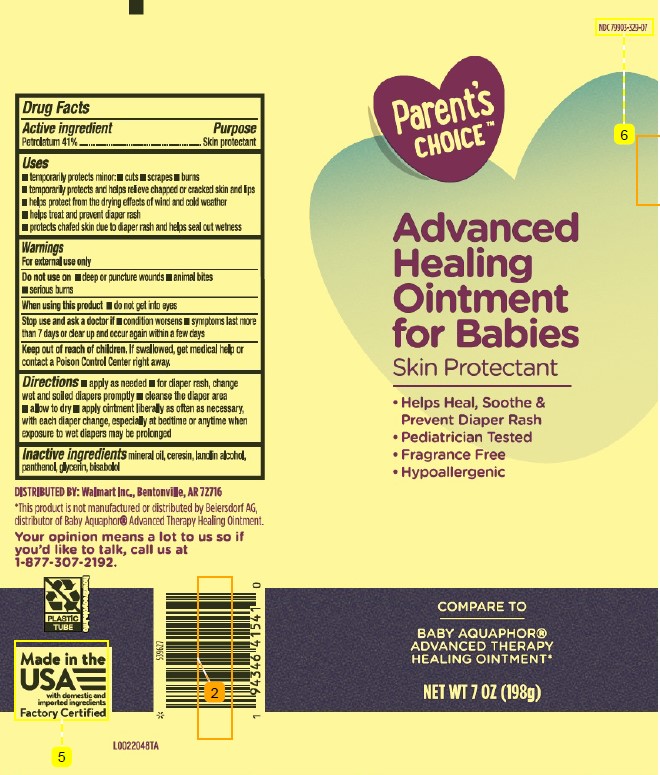 DRUG LABEL: Skin Protectant
NDC: 79903-329 | Form: OINTMENT
Manufacturer: Walmart Inc.
Category: otc | Type: HUMAN OTC DRUG LABEL
Date: 20260227

ACTIVE INGREDIENTS: PETROLATUM 410 mg/1 g
INACTIVE INGREDIENTS: MINERAL OIL; CERESIN; LANOLIN ALCOHOLS; PANTHENOL; GLYCERIN; LEVOMENOL

Parents Choice 180.000/180AC
Healing Ointment for Babies

Active Ingredient

Petrolatum 41%

PURPOSE

Skin protectant

Uses

■ temporarily protects minor: ■ cuts ■ scrapes ■ burns
■ temporarily protects and helps relieve chapped or cracked skin and lips
■ helps protect from the drying effects of wind and cold weather
■ helps treat and prevent diaper rash
■ protects chafed skin due to diaper rash and helps seal out wetness

Warnings

For external use only

Do not use on

- deep or puncture wounds
- animal bites
- serious burns

When using this product

- do not get into eyes

Stop use and ask a doctor if

- condition worsens
- symptoms last more than 7 days or clear up and occur again within a few days

KEEP OUT OF REACH OF CHILDREN.

If swallowed, get medical help or contact a Poison Control Center right away.

Directions

■ apply as needed
■ for diaper rash, change wet and soiled diapers promptly
■ cleanse the diaper area
■ allow to dry
■ apply ointment liberally as often as necessary, with each diaper change, especially at bedtime or anytime when exposure to wet diapers may be prolonged

INACTIVE INGREDIENTS

mineral oil, ceresin, lanolin alcohol, panthenol, glycerin, bisabolol

Disclaimer

*This product is not manufactured or distributed by Beiersorf AG, distributor of Baby Aquaphor®Advanced Therapy Healing Ointment.

ADVERSE REACTION

DISTRIBUTED BY: Walmart Inc., Bentonville, AR 72716

Your opinion means a lot to us so if you'd like to talk, call us at 1-877-307-2192.

PLASTIC TUBE

how2recycle.info

Made in the USA with domestic and imported ingredients

Factory Certified

PRINCIPAL DISPLAY PANEL

NDC 79903-329-07

Parent's CHOICE™

Advanced

Healing

Ointment

for Babies

Skin Protectant

- Helps Heal, Soothe & Prevent Diaper Rash
- Pediatrician Tested
- Fragrance Free
- Hypoallergenic

COMPARE TO

BABY AQUAPHOR®

ADVANCED THERAPY

HEALING OINTMENT*

NET WT 7 OZ (198g)